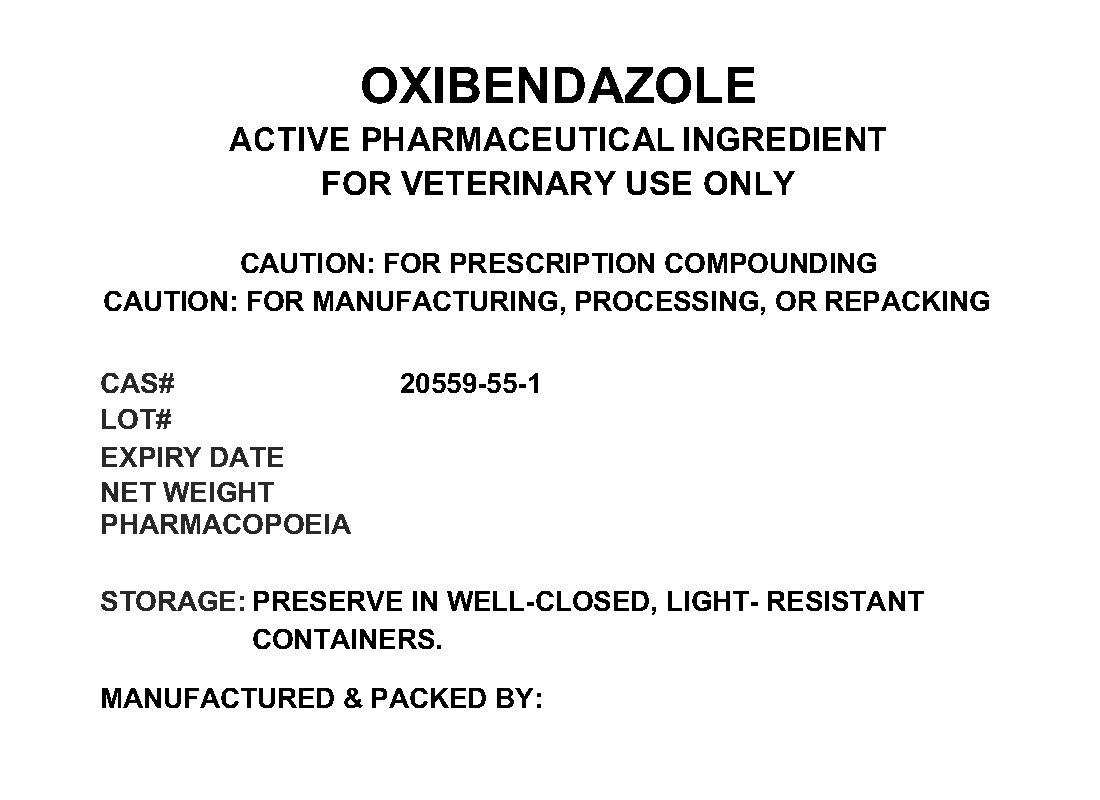 DRUG LABEL: OXIBENDAZOLE
NDC: 72969-117 | Form: POWDER
Manufacturer: PROFESSIONAL GROUP OF PHARMACISTS NEW YORK LLC
Category: other | Type: BULK INGREDIENT
Date: 20211221

ACTIVE INGREDIENTS: OXIBENDAZOLE 1 g/1 g

OXIBENDAZOLE

PACKAGE LABEL

oxibendazolelabel.jpg